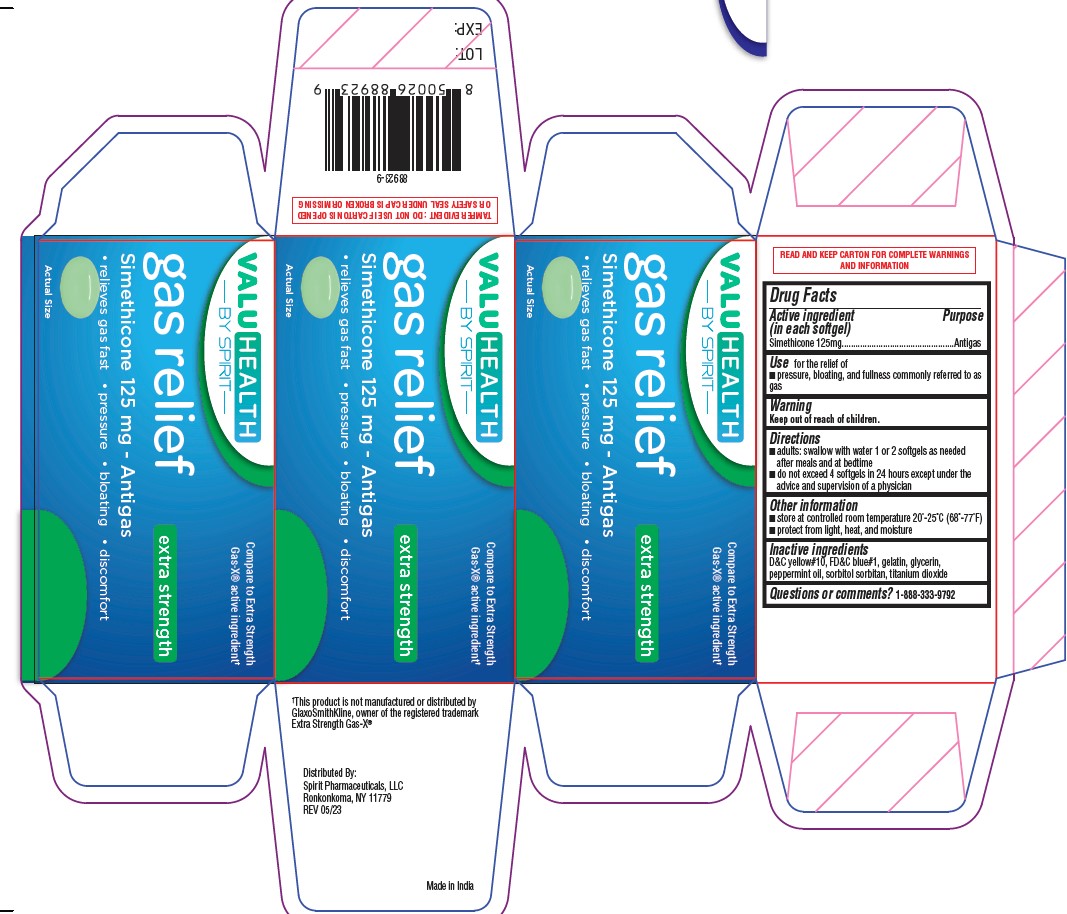 DRUG LABEL: Gas Relief
NDC: 68210-5026 | Form: CAPSULE, LIQUID FILLED
Manufacturer: Spirit Pharmaceuticals LLC
Category: otc | Type: HUMAN OTC DRUG LABEL
Date: 20241213

ACTIVE INGREDIENTS: DIMETHICONE 125 mg/1 1
INACTIVE INGREDIENTS: FD&C BLUE NO. 1; GELATIN; GLYCERIN; PEPPERMINT OIL; SORBITOL SOLUTION; TITANIUM DIOXIDE; D&C YELLOW NO. 10

ValuHealth By Spirit Gas relief

Active Ingredients (in each softgel)

Simethicone 125 mg

Purpose

Antigas

INDICATIONS AND USAGE

Use for the relief of

- pressure, bloating, and fullness commonly referred to as gas

Directions

- adults:swallow with water 1 or 2 softgels as needed after meals and at bedtime
- do not exceed 4 softgels in 24 hours except under the advice and supervision of a physician

other information

- store at controlled room temperature 20°-25°C (68°-77°F)
- protact from light, heat and moisture

Inactive ingredients

D&C yellow#10, FD&C blue#1, gelatin, glycerin, peppermint oil, sorbitol sorbitan, titanium dioxide

Questions or comments? 1-888-333-9792